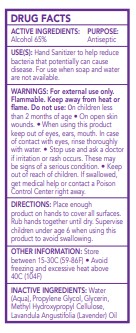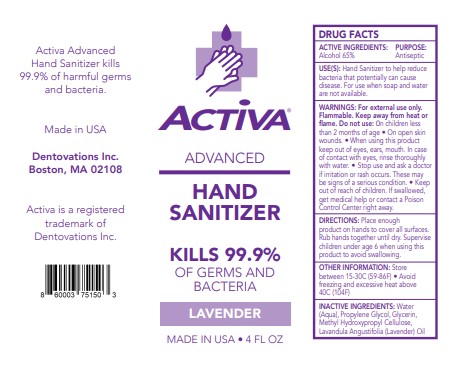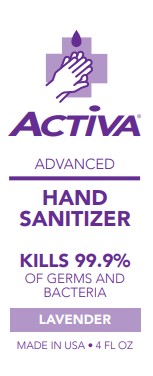 DRUG LABEL: Dentovations
NDC: 73333-113 | Form: LIQUID
Manufacturer: Nutrix international, LLC.
Category: otc | Type: HUMAN OTC DRUG LABEL
Date: 20200502

ACTIVE INGREDIENTS: ALCOHOL 0.65 g/113 g
INACTIVE INGREDIENTS: GLYCERIN 0.01 g/113 g; WATER 0.322 g/113 g; HYPROMELLOSES 0.0075 g/113 g; LAVENDER OIL 0.0005 g/113 g; PROPYLENE GLYCOL 0.01 g/113 g

Active ingredient[s]

Alcohol 65%v/v

Use[s]

Hand Sanitizer to help reduce bacteria that potentially can cause disease. For use when soap and water are not available.

Warnings

For external use only. Flammable . Keep away from heat or flame.

Do not use

- On children less than 2 months of age.
- On open skin wounds.

When using

When using this product keep out of eyes, ears, mouth. In case of contact with eyes, rinse thoroughly with water.

Stop use section and ask a doctor if irritation or rash occurs.

Keep out of reach of children. If swallowed, get medical help or contact a Poison Control Center right away.

Purpose

Antiseptic

Directions

- Place enough product on hands to cover all surfaces.
- Rub hands together until dry.
- Supervise children under age of 6 when using this product to avoid swallowing.

Other Information

- Store between 15-30°C (59-86°F)
- Avoid freezing and excessive heat above 40°C (104°F)

Inactive Ingredients

Water (Aqua), Propylene Glycol, Glycerin, Methyl hydroxypropyl Cellulose, Lavandula Angustifolia (lavender Oil)

Front label